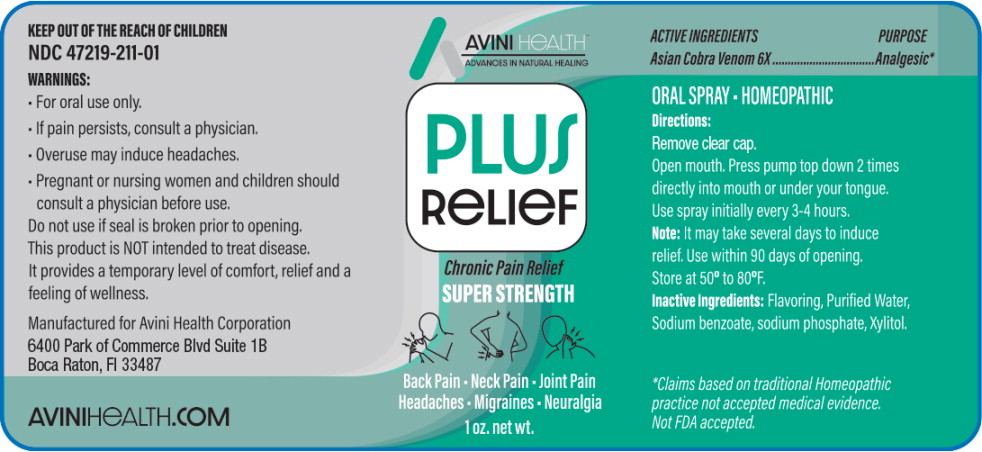 DRUG LABEL: Plus Relief
NDC: 47219-211 | Form: SPRAY, METERED
Manufacturer: Nutra Pharma Corporation
Category: homeopathic | Type: HUMAN OTC DRUG LABEL
Date: 20251103

ACTIVE INGREDIENTS: NAJA NAJA VENOM 6 [hp_X]/1 mL
INACTIVE INGREDIENTS: WATER; SODIUM BENZOATE; SODIUM PHOSPHATE; XYLITOL

Drug Facts

ACTIVE INGREDIENTS

Analgesic*

PURPOSE

Asian Cobra Venom 6X

*Claims based on traditional Homeopathic practice not accepted medical evidence. Not FDA accepted.

INDICATIONS AND USAGE

ORAL SPRAY-HOMEOPATHIC

Directions:

Remove clear cap.

Open mouth. Press pump top down 2 times directly into mouth or under your tongue. Use spray initially every 3-4 hours.

Note:It may take several days to induce relief. Use within 90 days of opening.
Store at 50° to 80°F.

KEEP OUT OF THE REACH OF CHILDREN

NDC 47219-211-01

WARNINGS:

- For oral use only.
- If pain persists, consult a physician.
- Overuse may induce headaches.
- Pregnant or nursing women and children should consult a physician before use.

Do not use if seal is broken prior to opening.

This product is NOT intended to treat disease.

It provides a temporary level of comfort, relief and a feeling of wellness.

Inactive Ingredients:

Flavoring, Purified Water, Sodium benzoate, sodium phosphate, Xylitol.

Principal Display Panel - 1 oz Bottle Label

AVINIHEALTH ™
ADVANCES IN NATURAL HEALING

PLUS
RELIEF

Chronic Pain Relief

SUPER STRENGTH

Back Pain-Neck Pain-Joint Pain
Headaches ■ Migraines ■ Neuralgia

1 oz. net wt.